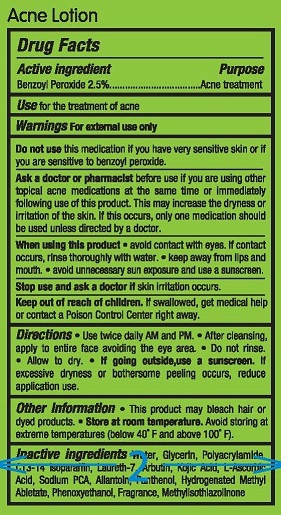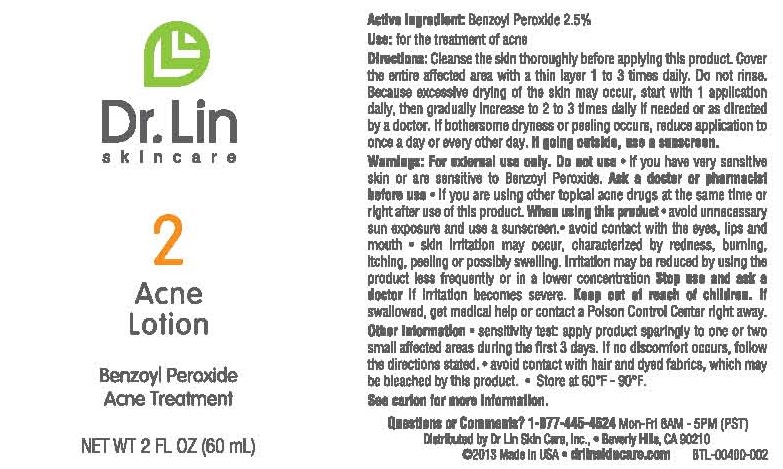 DRUG LABEL: DR. LIN SKINCARE ACNE
NDC: 58876-104 | Form: LOTION
Manufacturer: DR LIN SKINCARE
Category: otc | Type: HUMAN OTC DRUG LABEL
Date: 20130628

ACTIVE INGREDIENTS: BENZOYL PEROXIDE 2.5 g/100 mL
INACTIVE INGREDIENTS: WATER; GLYCERIN; POLYACRYLAMIDE (1500 MW); C13-14 ISOPARAFFIN; LAURETH-7; ARBUTIN; KOJIC ACID; ASCORBIC ACID; SODIUM PYRROLIDONE CARBOXYLATE; ALLANTOIN; PANTHENOL; GLYCERYL ABIETATE; PHENOXYETHANOL; METHYLISOTHIAZOLINONE

ACTIVE INGREDIENT

BENZOYL PEROXIDE 2.5%

PURPOSE

ACNE TREATMENT

WARNINGS

FOR EXTERNAL USE ONLY

DO NOT USE THIS MEDICATION IF YOU HAVE VERY SENSITIVE SKIN OR IF YOU ARE SENSITIVE TO BENZOYL PEROXIDE.

ASK A DOCTOR OR PHARMACIST BEFORE USE IF YOU ARE USING OTHER TOPCAL ACNE MEDICATONS AT THE SAME TIME OR IMMEDIATELY FOLLOWING USE OF THIS PRODUCT. THIS MAY INCREASETHE DRYNESS OR IRRITATION OF THE SKIN. IF THIS OCCURS, ONLY ONEMEDICATION SHOULD BE USED UNLESS DIRECTED BY A DOCTOR.

WHEN USING THIS PRODUCT

- AVOID CONTACT WTH EYES. IF CONTACT OCCURS, RINSE THOROUGHLY WITH WATER.
- KEEP AWAY FROM LIPS AND MOUTH.
- AVOID UNNECESSARY SUN EXPOSURE AND USE A SUNSCREEN.

STOP USE AND ASK A DOCTOR IF SKIN IRRITATION OCCURS.

KEEP OUT OF REACH OF CHILDREN. IF SWALLOWED, GET MEDICAL HELP OR CONTACT A POISON CONTROL CENTER RIGHT AWAY.

INDICATIONS AND USAGE

USE FOR THE TREATMENT OF ACNE

DIRECTIONS

- USE TWICE DAILY AM AND PM.
- AFTER CLEANSING, APPLY TO ENTIRE FACE AVOIDING THE EYE AREA.
- DO NOT RINSE.
- ALLOW TO DRY.
- IF GOING OUTSIDE, USE A SUNSCREEN. IF EXCESSIVE DRYNESS OR BOTHERSOME PEELING OCCURS, REDUCE APPLICATION USE.

OTHER INFORMATION

- THIS PRODUCT MAY BLEACH HAIR OR DYED FABRICS.
- STORE AT ROOM TEMPERATURE.
- AVOID STORING AT EXTREME TEMPERATURES (BELOW 40°F AND ABOVE 100°F).

INACTIVE NGREDIENTS

WATER, GLYCERIN, POLYACRYLAMIDE, C13-14 ISOPARAFFIN, LAURETH-7, ARBUTIN, KOJIC ACID, L-ASCORBIC ACID, SODIUM PCA, ALLANTOIN, PANTHENOL, HYDROGENATED METHYL ABIETATE, PHENOXYETHANOL, FRAGRANCE, METHYLISOTHIAZOLINONE